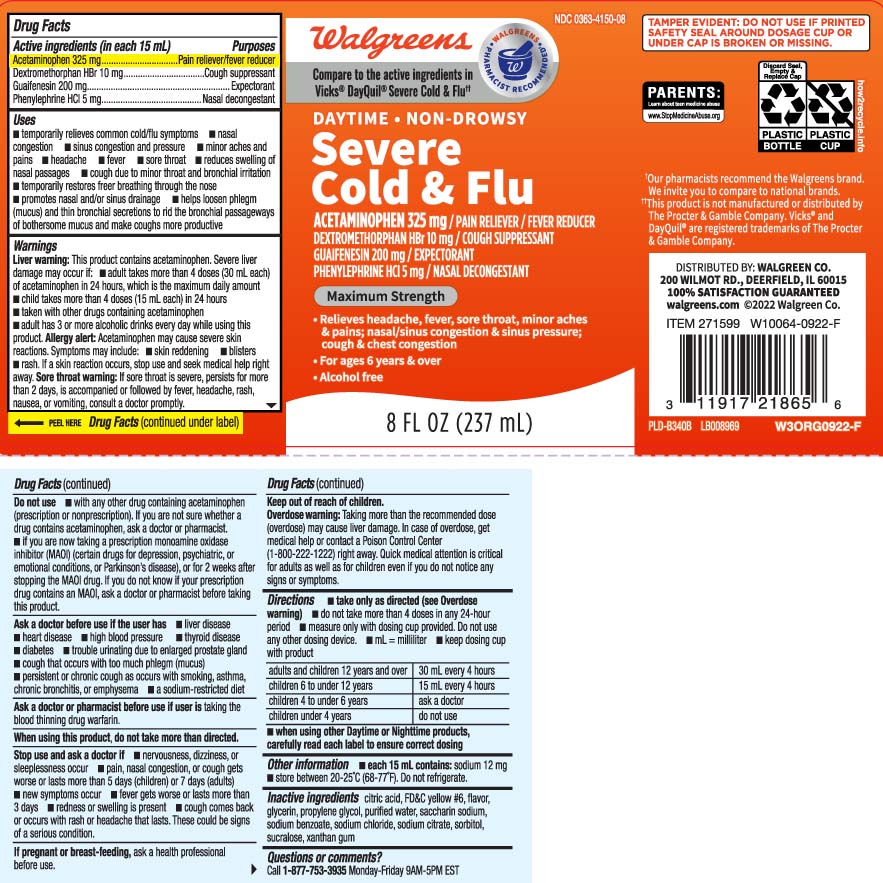 DRUG LABEL: Severe Cold and Flu Relief
NDC: 0363-4150 | Form: LIQUID
Manufacturer: Walgreens
Category: otc | Type: HUMAN OTC DRUG LABEL
Date: 20251216

ACTIVE INGREDIENTS: ACETAMINOPHEN 325 mg/15 mL; DEXTROMETHORPHAN HYDROBROMIDE 10 mg/15 mL; GUAIFENESIN 200 mg/15 mL; PHENYLEPHRINE HYDROCHLORIDE 5 mg/15 mL
INACTIVE INGREDIENTS: FD&C YELLOW NO. 6; GLYCERIN; PROPYLENE GLYCOL; WATER; SORBITOL; SACCHARIN SODIUM; SODIUM BENZOATE; SODIUM CHLORIDE; SODIUM CITRATE; XANTHAN GUM; SUCRALOSE; ANHYDROUS CITRIC ACID

Drug Facts

Active ingredients (in each 15 mL)

Acetaminophen 325 mg

Dextromethorphan HBr 10 mg

Guaifenesin 200 mg

Phenylephrine HCl 5 mg

Purpose

Pain reliever/fever reducer

Cough suppressant

Expectorant

Nasal decongestant

Uses

- temporarily relieves common cold and flu symptoms:
  - nasal congestion
  - sinus congestion and pressure
  - minor aches and pains
  - headache
  - fever
  - sore throat
  - reduces swelling of nasal passages
  - cough due to minor throat and bronchial irritation
  - temporarily restores freer breathing through the nose
  - promotes nasal and or sinus drainage
  - helps loosen phlegn (mucus) and thin bronchial secretions to rid the bronchial passageways of bothersome mucus and make cough more productive

Warnings

Liver warning: This product contains acetaminophen. Severe liver damage may occur if you take

- adult take more than 4 doses (30 mL each) of acetaminophen in 24 hours, which is the maximum daily amount
- child takes more than 4 doses (15 mL each) in 24 hours
- taken with other drugs containing acetaminophen
- adult has 3 or more alcoholic drinks every day while using this product

Allergy alert: Acetaminophen may cause severe skin reactions. Symptoms may include:

- skin reddening
- blistere
- rash.

If a skin reaction occurs, stop use and seek medical help right away.

Sore throat warning: If sore throat is severe, persists for more than 2 days, is accompanied or is followed by fever, headache, rash, nausea, or vomiting, consult a doctor promptly.

Do not use

- with any other drug containing acetaminophen (prescription or nonprescription). If you are not sure whether a drug contains acetaminophen, ask a doctor or pharmacist.
- if you are now taking a prescription monoamine oxidase inhibitor (MAOI) (certain drugs for depression, psychiatric or emotional conditions, or Parkinson’s disease), or for 2 weeks after stopping the MAOI drug. If you do not know if your prescription drug contains an MAOI, ask a doctor or pharmacist before taking this product.

Ask a doctor before use if you have

- liver disease
- heart disease
- high blood pressure
- thyroid disease
- diabetes
- trouble urinating due to an enlarged prostate gland
- cough that occurs with too much phlegm (mucus)
- persistent or chronic cough as occurs with smoking, asthma, chronic bronchitis, or emphysema
- a sodium restricted diet

Ask a doctor or pharmacist before use if user is

taking the blood thinning drug warfarin

When using this product

do not take more than directed.

Stop use and ask a doctor if

- nervousness, dizziness, or sleeplessness occur
- pain, nasal congestion, or cough gets worse or lasts more than 5 days (children) or 7 days (adults)
- new symptoms occur
- fever gets worse or lasts more than 3 days
- redness or swelling is present
- cough comes back or occurs with rash or headache that lasts. These could be signs of a serious condition.

If pregnant or breast-feeding,

ask a health professional before use.

Keep out of reach of children.

Overdose warning: Taking more than the recommended dose can cause serious liver damage.In case of overdose, get medical help or contact a Poison Control Center (1-800-222-1222) right away. Quick medical attention is critical for adults and for children even if you do not notice any signs or symptoms

Directions

- take only as directed (see overdose warning)
- do not take more than 4 doses in any 24 hours
- measure only with dosing cup provided. Do not use any other dosing device
- mL = milliliter
- keep dosing cup with product

adults and children12 years and over | 30 mL every 4 hours
children 6 to under 12 years | 15 mL every 4 hours
children 4 to under 6 years | ask a doctor
children under 4 years | do not use

- when using other Daytime or Nighttime products, carefully read each label to ensure correct dosing

Other information

- each 15 mL contains: sodium 12 mg
- store between 20-25ºC (68-77ºF). Do not refrigerate.

Inactive ingredients

citric acid, FD&C Yellow #6, flavor, glycerin, propylene glycol, purified water, saccharin sodium, sodium benzoate sodium chloride, sodium citrate, sorbitol sucralose, xanthan gum

Questions or comments?

Call 1-877-753-3935 Monday-Friday 9AM-5PM EST

Principal Display Panel

Compare to the active ingredients in Vicks® DayQuil® Severe Cold & Flu††

DAYTIME • NON-DROWSY

Severe Cold & Flu Relief

ACETAMINOPHEN 325 mg /PAIN RELIEVER/FEVER REDUCER

DEXTROMETHORPHAN HBr 10 mg / COUGH SUPPRESSANT

GUAIFENESIN 200 mg / EXPECTORANT

PHENYLEPHRINE HCl 5 mg / NASAL CONGESTION

MAXIMUM STRENGTH

- Relieves headache, fever, sore throat, minor aches & pain; nasal/sinus congestion & sinus pressure; cpough & chest congestion
- For ages 6 years & over
- Alcohol free

FL OZ (mL)

††This product is not manufactured or distributed by The Procter & Gamble Company. Vicks® and DayQuil® are registered trademarks of The Procter & Gamble Company.

TAMPER EVIDENT: DO NOT USE IF PRINITED SAFETY SEAL AROUND DOSAGE CUP OR UNDER CAP IS BROKEN OR MISSING.

DISTRIBUTED BY: WALGREEN CO.

200 WILMOT RD., DEERFIELD, IL 60015

Product Label

WALGREENS DayTime Non-Drowsy Severe Cold & Flu